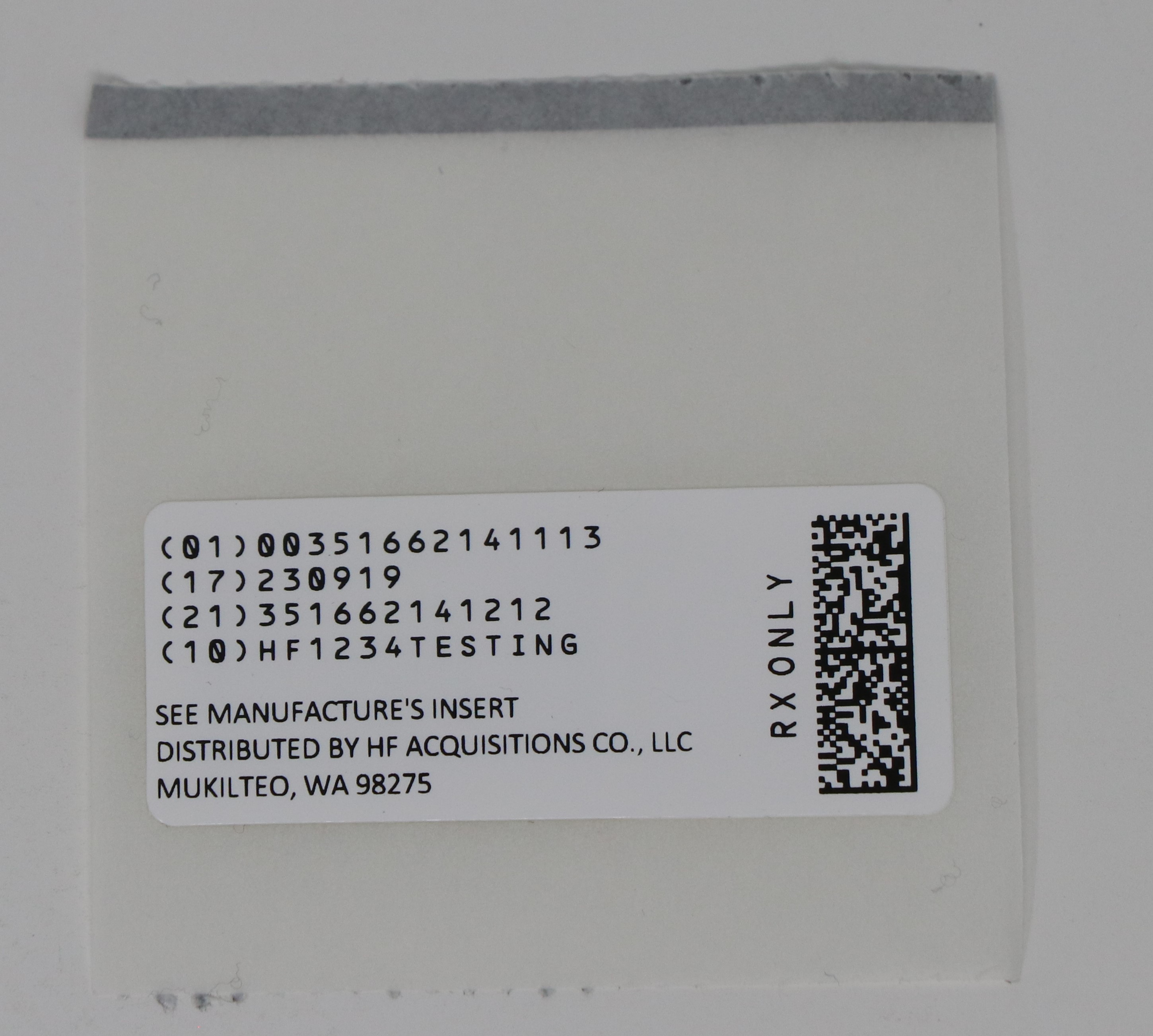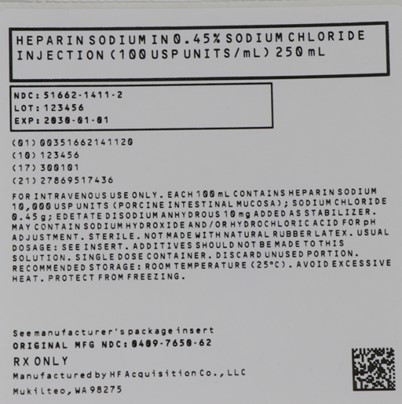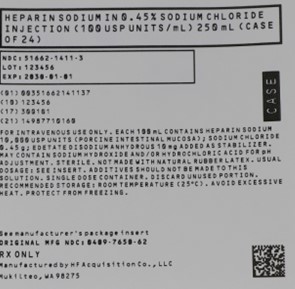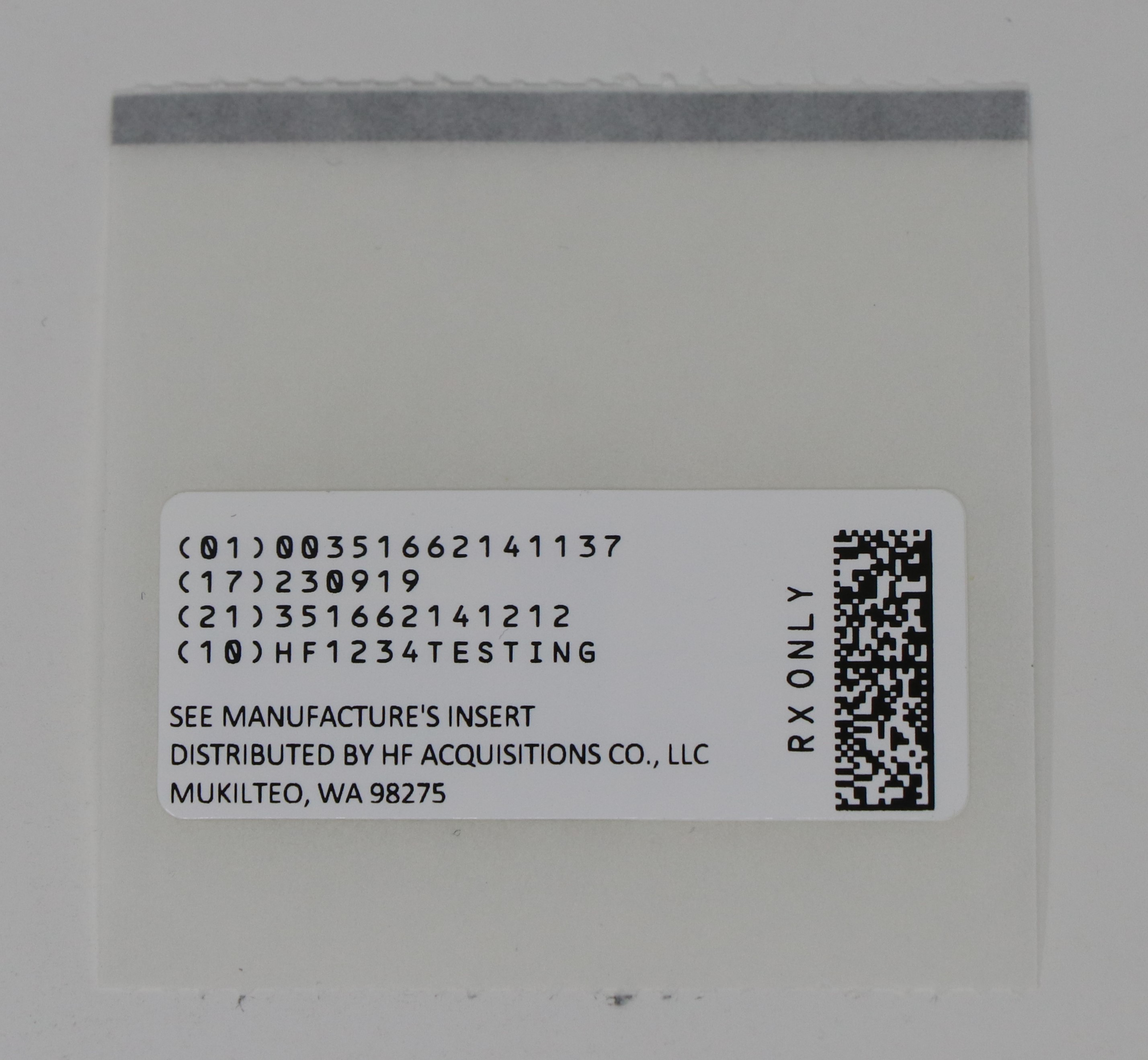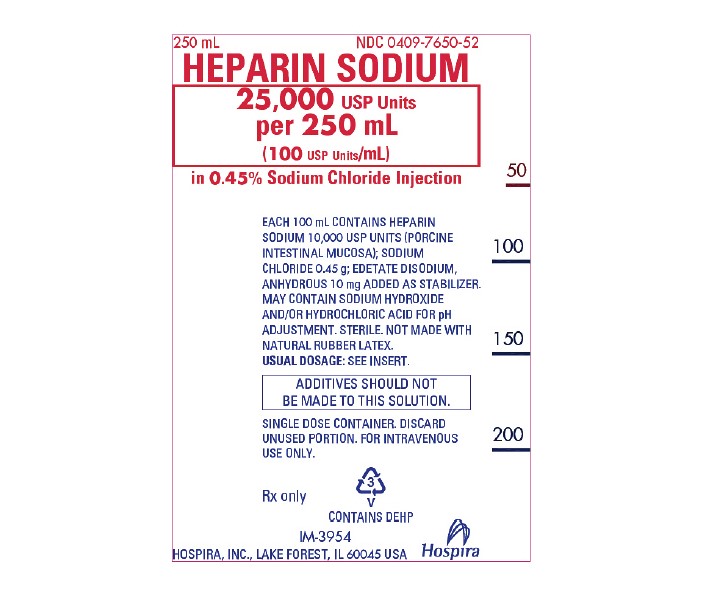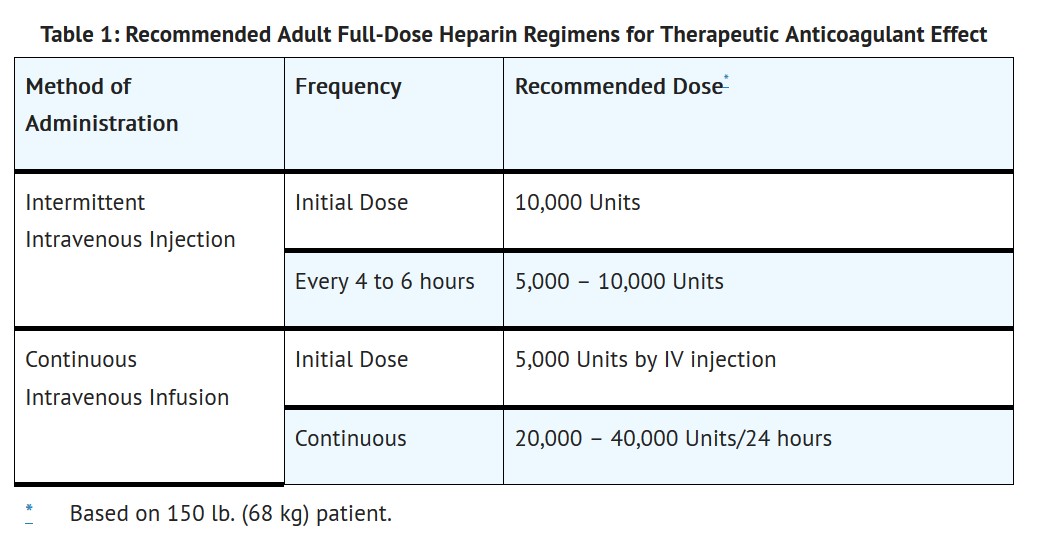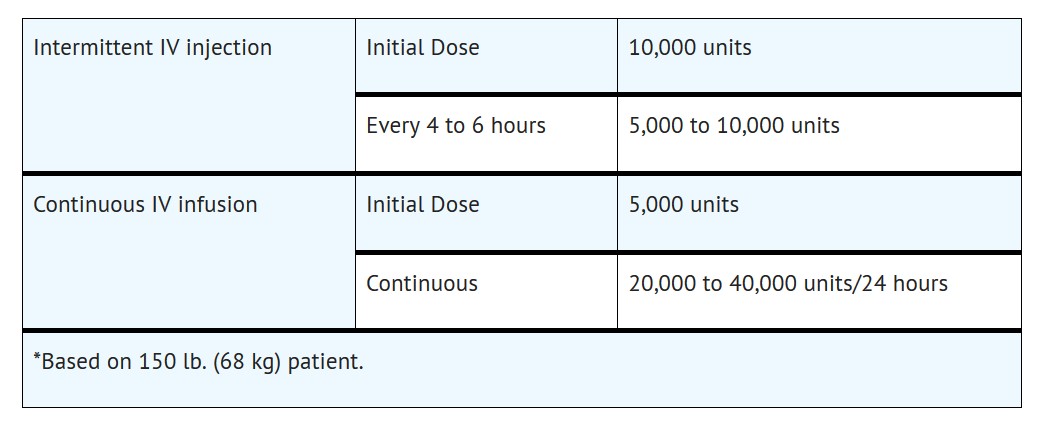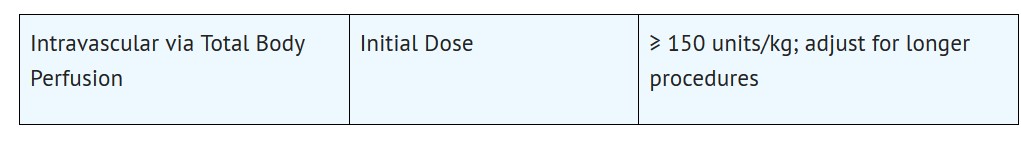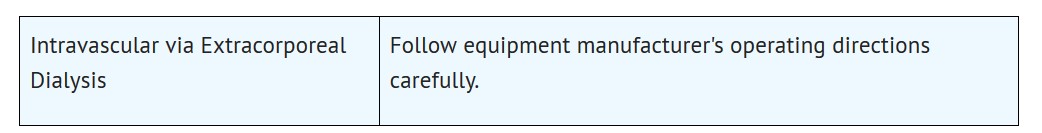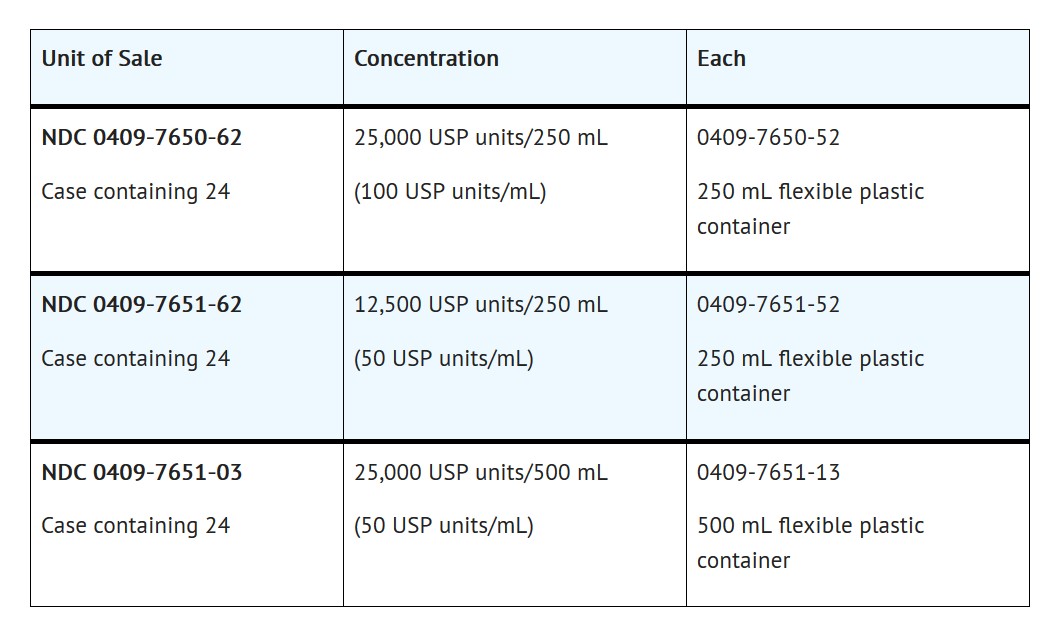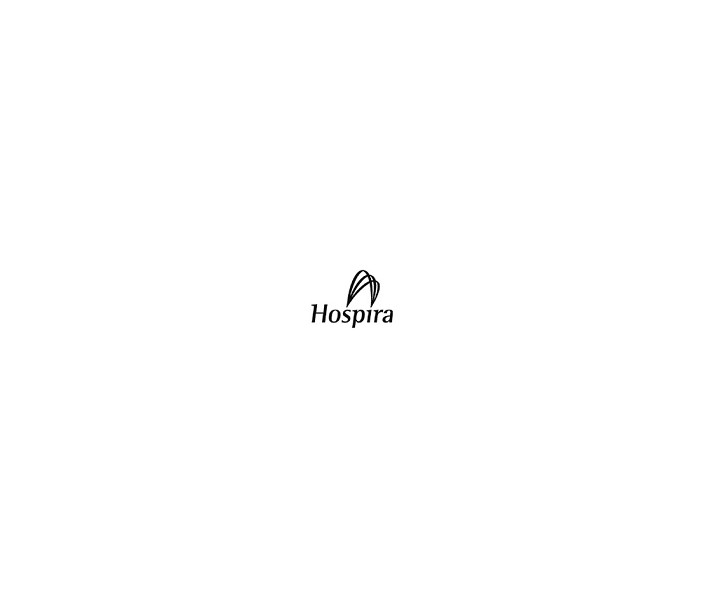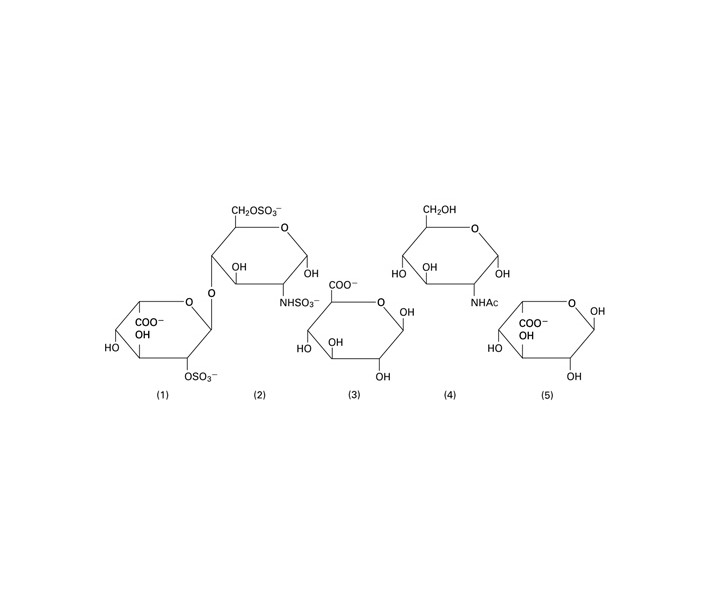 DRUG LABEL: HEPARIN SODIUM
NDC: 51662-1411 | Form: INJECTION, SOLUTION
Manufacturer: HF Acquisition Co LLC, DBA HealthFirst
Category: prescription | Type: HUMAN PRESCRIPTION DRUG LABEL
Date: 20240125

ACTIVE INGREDIENTS: HEPARIN SODIUM 10000 [USP'U]/100 mL
INACTIVE INGREDIENTS: SODIUM HYDROXIDE; HYDROCHLORIC ACID; WATER; SODIUM CHLORIDE 0.45 g/100 mL; EDETATE DISODIUM ANHYDROUS 10 mg/100 mL

HEPARIN SODIUM IN 0.45% SODIUM CHLORIDE INJECTION (100 USP UNITS/mL) 250 mL

HIGHLIGHTS OF PRESCRIBING INFORMATION

These highlights do not include all the information needed to use HEPARIN SODIUM IN 0.45% SODIUM CHLORIDE INJECTION safely and effectively. See full prescribing information for HEPARIN SODIUM IN 0.45% SODIUM CHLORIDE INJECTION.
HEPARIN SODIUM IN 0.45% SODIUM CHLORIDE INJECTION, for intravenous use
Initial U.S. Approval: 1939

INDICATIONS AND USAGE

Heparin sodium is indicated for: (1)

•
Prophylaxis and treatment of venous thromboembolism
•
Prophylaxis and treatment of the thromboembolic complications associated with atrial fibrillation
•
Treatment of acute and chronic consumption coagulopathies
•
Prevention of clotting in arterial and cardiac surgery
•
Prophylaxis and treatment of peripheral arterial embolism
•
Anticoagulant use in extracorporeal circulation and dialysis procedure

DOSAGE AND ADMINISTRATION

Recommended Adult Dosages:

•
Therapeutic Anticoagulant Effect with Full-Dose Heparin* (2-2.3)

• Surgery of the Heart and Blood Vessels (2-2.5)

Extracorporeal Dialysis (2-2.8)

DOSAGE FORMS AND STRENGTHS

•
Heparin sodium is available as: (3)
•
Injection: 100 USP Units/mL in 0.45% Sodium Chloride clear solution (25,000 USP Units/250 mL) in single-dose plastic container
•
Injection: 50 USP Units/mL in 0.45% Sodium Chloride clear solution (12,500 USP Units/250 mL) in single-dose plastic container
•
Injection: 50 USP Units/mL in 0.45% Sodium Chloride clear solution (25,000 USP Units/500 mL) in single-dose plastic container

CONTRAINDICATIONS

•
History of Heparin-induced Thrombocytopenia (HIT) (With or Without Thrombosis) (4)
•
Known hypersensitivity to heparin or pork products (4)
•
In whom suitable blood coagulation tests cannot be performed at appropriate intervals (4)

WARNINGS AND PRECAUTIONS

•
Fatal Medication Errors: Confirm choice of correct strength prior to administration. (5-5.1)
•
Hemorrhage: Fatal cases have occurred. Use caution in conditions with increased risk of hemorrhage. 5-(5.2)
•
HIT (With or Without Thrombosis): Monitor for signs and symptoms and discontinue if indicative of HIT (With or Without Thrombosis). (5-5.3)
•
Monitoring: Blood coagulation tests guide therapy for full-dose heparin.
Monitor platelet count and hematocrit in all patients receiving heparin. (5-5.5)

ADVERSE REACTIONS

Most common adverse reactions are hemorrhage, thrombocytopenia, HIT (With or Without Thrombosis), injection site irritation, general hypersensitivity reactions, and elevations of aminotransferase levels (6-6.1)

To report SUSPECTED ADVERSE REACTIONS, contact Hospira, Inc. at 1-800-441-4100, or FDA at 1-800-FDA-1088 or www.fda.gov/medwatch.

DRUG INTERACTIONS

•
Drugs that interfere with platelet aggregation: May induce bleeding. (7-7.2)

See 17 for PATIENT COUNSELING INFORMATION.

Revised: 3/2016

TABLE OF CONTENTS

FULL PRESCRIBING INFORMATION: CONTENTS*
1 INDICATIONS AND USAGE
2 DOSAGE AND ADMINISTRATION
2.1 Preparation for Administration
2.2 Laboratory Monitoring for Efficacy and Safety
2.3 Therapeutic Anticoagulant Effect with Full-Dose Heparin
2.4 Pediatric Use
2.5 Cardiovascular Surgery
2.6 Converting to Warfarin
2.7 Converting to Oral Anticoagulants other than Warfarin
2.8 Extracorporeal Dialysis
3 DOSAGE FORMS AND STRENGTHS
4 CONTRAINDICATIONS
5 WARNINGS AND PRECAUTIONS
5.1 Fatal Medication Errors
5.2 Hemorrhage
5.3 Heparin-induced Thrombocytopenia (HIT) (With or Without Thrombosis)
5.4 Thrombocytopenia
5.5 Coagulation Testing and Monitoring
5.6 Heparin Resistance
5.7 Hypersensitivity
6 ADVERSE REACTIONS
6.1 Postmarketing Experience
7 DRUG INTERACTIONS
7.1 Oral Anticoagulants
7.2 Platelet Inhibitors
7.3 Other Interactions
7.4 Drug/Laboratory Test Interactions
8 USE IN SPECIFIC POPULATIONS
8.1 Pregnancy
8.2 Lactation
8.4 Pediatric Use
8.5 Geriatric Use
10 OVERDOSAGE
11 DESCRIPTION
12 CLINICAL PHARMACOLOGY
12.1 Mechanism of Action
12.2 Pharmacodynamics
12.3 Pharmacokinetics
13 NONCLINICAL TOXICOLOGY
13.1 Carcinogenesis, Mutagenesis, Impairment of Fertility
16 HOW SUPPLIED/STORAGE AND HANDLING
17 PATIENT COUNSELING INFORMATION

*
Sections or subsections omitted from the full prescribing information are not listed.

1 INDICATIONS & USAGE

Heparin sodium is indicated for:

•
Prophylaxis and treatment of venous thrombosis and pulmonary embolism;
•
Prophylaxis and treatment of thromboembolic complications associated with atrial fibrillation;
•
Treatment of acute and chronic consumption coagulopathies (disseminated intravascular coagulation);
•
Prevention of clotting in arterial and cardiac surgery;
•
Prophylaxis and treatment of peripheral arterial embolism;
•
Anticoagulant use in blood transfusions, extracorporeal circulation, and dialysis procedures.

2 DOSAGE & ADMINISTRATION

2.1 Preparation for Administration

Confirm the selection of the correct formulation and strength prior to administration of the drug. Do not use Heparin Sodium in 0.45% Sodium Chloride Injection as a "catheter lock flush" product.

Administer this product by intravenous infusion.

Do not admix with other drugs.

Do not use flexible container in series connections.

Parenteral drug products should be inspected visually for particulate matter and discoloration prior to administration, whenever solution and container permit.

2.2 Laboratory Monitoring for Efficacy and Safety

Adjust the dosage of heparin sodium according to the patient's coagulation test results. When heparin is given by continuous intravenous infusion, determine the coagulation time approximately every 4 hours in the early stages of treatment. When the drug is administered intermittently by intravenous injection, perform coagulation tests before each injection during the early stages of treatment and at appropriate intervals thereafter. Dosage is considered adequate when the activated partial thromboplastin time (APTT) is 1.5 to 2 times the normal or when the whole blood clotting time is elevated approximately 2.5 to 3 times the control value.

Periodic platelet counts, hematocrits, and tests for occult blood in stool are recommended during the entire course of heparin therapy.

2.3 Therapeutic Anticoagulant Effect with Full-Dose Heparin

The dosing recommendations in Table 1 are based on clinical experience. Although dosage must be adjusted for the individual patient according to the results of suitable laboratory tests, the following dosage schedules may be used as guidelines:

Table 1: Recommended Adult Full-Dose Heparin Regimens for Therapeutic Anticoagulant Effect

2.4 Pediatric Use

There are no adequate and well controlled studies on heparin use in pediatric patients. Pediatric dosing recommendations are based on clinical experience. In general, the following dosage schedule may be used as a guideline in pediatric patients:

Initial Dose 75 to 100 units/kg (IV bolus over 10 minutes)
Maintenance Dose Infants: 25 to 30 units/kg/hour;
Infants < 2 months have the highest requirements (average 28 units/kg/hour)
Children > 1 year of age: 18 to 20 units/kg/hour;
Older children may require less heparin, similar to weight-adjusted adult dosage
Monitoring Adjust heparin to maintain a PTT of 60 to 85 seconds, assuming this reflects an
anti-Factor Xa level of 0.35 to 0.70.

2.5 Cardiovascular Surgery

Patients undergoing total body perfusion for open-heart surgery should receive an initial dose of not less than 150 units of heparin sodium per kilogram of body weight. Frequently, a dose of 300 units per kilogram is used for procedures estimated to last less than 60 minutes or 400 units per kilogram for those estimated to last longer than 60 minutes.

2.6 Converting to Warfarin

To ensure continuous anticoagulation when converting from HEPARIN SODIUM to warfarin, continue full heparin therapy for several days until the INR (prothrombin time) has reached a stable therapeutic range. Heparin therapy may then be discontinued without tapering [see Drug Interactions (7.4)].

2.7 Converting to Oral Anticoagulants other than Warfarin

For patients currently receiving intravenous heparin, stop intravenous infusion of heparin sodium immediately after administering the first dose of oral anticoagulant; or for intermittent intravenous administration of heparin sodium, start oral anticoagulant 0 to 2 hours before the time that the next dose of heparin was to have been administered.

2.8 Extracorporeal Dialysis

Follow equipment manufacturer's operating directions carefully. A dose of 25 to 30 units/kg followed by an infusion rate of 1,500 to 2,000

2.4 Pediatric Use

There are no adequate and well controlled studies on heparin use in pediatric patients. Pediatric dosing recommendations are based on clinical experience. In general, the following dosage schedule may be used as a guideline in pediatric patients:

Initial Dose 75 to 100 units/kg (IV bolus over 10 minutes)
Maintenance Dose Infants: 25 to 30 units/kg/hour;
Infants < 2 months have the highest requirements (average 28 units/kg/hour)
Children > 1 year of age: 18 to 20 units/kg/hour;
Older children may require less heparin, similar to weight-adjusted adult dosage
Monitoring Adjust heparin to maintain a PTT of 60 to 85 seconds, assuming this reflects an
anti-Factor Xa level of 0.35 to 0.70.

2.5 Cardiovascular Surgery

Patients undergoing total body perfusion for open-heart surgery should receive an initial dose of not less than 150 units of heparin sodium per kilogram of body weight. Frequently, a dose of 300 units per kilogram is used for procedures estimated to last less than 60 minutes or 400 units per kilogram for those estimated to last longer than 60 minutes.

2.6 Converting to Warfarin

To ensure continuous anticoagulation when converting from HEPARIN SODIUM to warfarin, continue full heparin therapy for several days until the INR (prothrombin time) has reached a stable therapeutic range. Heparin therapy may then be discontinued without tapering [see Drug Interactions (7-7.4)].

2.7 Converting to Oral Anticoagulants other than Warfarin

For patients currently receiving intravenous heparin, stop intravenous infusion of heparin sodium immediately after administering the first dose of oral anticoagulant; or for intermittent intravenous administration of heparin sodium, start oral anticoagulant 0 to 2 hours before the time that the next dose of heparin was to have been administered.

2.8 Extracorporeal Dialysis

Follow equipment manufacturer's operating directions carefully. A dose of 25 to 30 units/kg followed by an infusion rate of 1,500 to 2,000 units/hour is suggested based on pharmacodynamic data if specific manufacturers' recommendations are not available.

3 DOSAGE FORMS & STRENGTHS

HEPARIN SODIUM IN 0.45% SODIUM CHLORIDE INJECTION is available as:

•
Injection: 100 USP Units/mL in 0.45% Sodium Chloride clear solution (25,000 USP Units/250 mL) in single-dose plastic container
•
Injection: 50 USP Units/mL in 0.45% Sodium Chloride clear solution (12,500 USP Units/250 mL) in single-dose plastic container
•
Injection: 50 USP Units/mL in 0.45% Sodium Chloride clear solution (25,000 USP Units/500 mL) in single-dose plastic container

4 CONTRAINDICATIONS

The use of HEPARIN SODIUM IN 0.45% SODIUM CHLORIDE INJECTION is contraindicated in patients:

•
With history of heparin-induced thrombocytopenia (HIT) (With or Without Thrombosis) [see WARNINGS AND PRECAUTIONS 5-(5.3)]
•
With a known hypersensitivity to heparin or pork products (e.g., anaphylactoid reactions) [see ADVERSE REACTIONS 6-(6.1)]
•
In whom suitable blood coagulation tests — e.g., the whole blood clotting time, partial thromboplastin time, etc., — cannot be performed at appropriate intervals (this contraindication refers to full-dose heparin; there is usually no need to monitor coagulation parameters in patients receiving low-dose heparin)

5 WARNINGS AND PRECAUTIONS

5.1 Fatal Medication Errors

Do not use this product as a "catheter lock flush" product. Heparin is supplied in various strengths. Fatal hemorrhages have occurred due to medication errors. Carefully examine all heparin products to confirm the correct container choice prior to administration of the drug.

5.2 Hemorrhage

Hemorrhage, including fatal events, has occurred in patients receiving HEPARIN SODIUM. Avoid using heparin in the presence of major bleeding, except when the benefits of heparin therapy outweigh the potential risks.

Hemorrhage can occur at virtually any site in patients receiving heparin. Adrenal hemorrhage (with resultant acute adrenal insufficiency), ovarian hemorrhage, and retroperitoneal hemorrhage have occurred during anticoagulant therapy with heparin [see ADVERSE REACTIONS 6-(6.1)]. A higher incidence of bleeding has been reported in patients, particularly women, over 60 years of age [see CLINICAL PHARMACOLOGY 12-(12.3)]. An unexplained fall in hematocrit or fall in blood pressure should lead to serious consideration of a hemorrhagic event.

Use heparin sodium with caution in disease states in which there is increased risk of hemorrhage, including:

•
Cardiovascular — Subacute bacterial endocarditis. Severe hypertension.
•
Surgical — During and immediately following (a) spinal tap or spinal anesthesia or (b) major surgery, especially involving the brain, spinal cord or eye.
•
Hematologic — Conditions associated with increased bleeding tendencies, such as hemophilia, thrombocytopenia and some vascular purpuras.
•
Patients with hereditary antithrombin III deficiency receiving concurrent antithrombin III therapy – The anticoagulant effect of heparin is enhanced by concurrent treatment with antithrombin III (human) in patients with hereditary antithrombin III deficiency. To reduce the risk of bleeding, reduce the heparin dose during concomitant treatment with antithrombin III (human).
•
Gastrointestinal — Ulcerative lesions and continuous tube drainage of the stomach or small intestine.
•
Other — Menstruation, liver disease with impaired hemostasis.

5.3 Heparin-induced Thrombocytopenia (HIT) (With or Without Thrombosis)

HIT is a serious antibody-mediated reaction resulting from irreversible aggregation of platelets. HIT may progress to the development of venous and arterial thromboses, a condition known as HIT with thrombosis. Thrombotic events may also be the initial presentation for HIT. These serious thromboembolic events include deep vein thrombosis, pulmonary embolism, cerebral vein thrombosis, limb ischemia, stroke, myocardial infarction, thrombus formation on a prosthetic cardiac valve, mesenteric thrombosis, renal arterial thrombosis, skin necrosis, gangrene of the extremities that may lead to amputation, and possibly death. Monitor thrombocytopenia of any degree closely. If the platelet count falls below 100,000/mm3 or if recurrent thrombosis develops, promptly discontinue heparin, evaluate for HIT, and, if necessary, administer an alternative anticoagulant.

HIT can occur up to several weeks after the discontinuation of heparin therapy. Patients presenting with thrombocytopenia or thrombosis after discontinuation of heparin should be evaluated for HIT.

5.4 Thrombocytopenia

Thrombocytopenia has been reported to occur in patients receiving heparin with a reported incidence of up to 30%. It can occur 2 to 20 days (average 5 to 9) following the onset of heparin therapy. Obtain platelet counts before and periodically during heparin therapy. Monitor thrombocytopenia of any degree closely. If the count falls below 100,000/mm3 or if recurrent thrombosis develops, promptly discontinue heparin, evaluate for HIT, and, if necessary, administer an alternative anticoagulant [see WARNINGS AND PRECAUTIONS 5-(5.3)].

5.5 Coagulation Testing and Monitoring

When using a full dose heparin regimen, adjust the heparin dose based on frequent blood coagulation tests. If the coagulation test is unduly prolonged or if hemorrhage occurs, heparin sodium should be discontinued promptly [see OVERDOSAGE 10]. Periodic platelet counts, hematocrits are recommended during the entire course of heparin therapy [see DOSAGE AND ADMINISTRATION 2-(2.2)].

5.6 Heparin Resistance

Increased resistance to heparin is frequently encountered in fever, thrombosis, thrombophlebitis, infections with thrombosing tendencies, myocardial infarction, cancer and in postsurgical patients, and patients with antithrombin III deficiency. Close monitoring of coagulation tests is recommended in these cases. Adjustment of heparin doses based on anti-Factor Xa levels may be warranted.

5.7 Hypersensitivity

Patients with documented hypersensitivity to heparin should be given the drug only in clearly life-threatening situations [see ADVERSE REACTIONS (6)]. Because heparin sodium is derived from animal tissue, monitor for signs and symptoms of hypersensitivity when it is used in patients with a history of allergy.

6 ADVERSE REACTIONS

The following serious adverse reactions are described elsewhere in the labeling:

•
Fatal Medication Errors [see WARNINGS AND PRECAUTIONS 5-(5.1)]
•
Hemorrhage [see WARNINGS AND PRECAUTIONS 5-(5.2)]
•
Heparin-induced Thrombocytopenia (HIT) (With or Without Thrombosis) [see WARNINGS AND PRECAUTIONS 5-(5.3)]
•
Thrombocytopenia [see WARNINGS AND PRECAUTIONS 5-(5.4)]
•
Heparin Resistance [see WARNINGS AND PRECAUTIONS 5-(5.6)]
•
Hypersensitivity [see WARNINGS AND PRECAUTIONS 5-(5.7)]

6.1 Postmarketing Experience

The following adverse reactions have been identified during post-approval use of heparin sodium. Because these reactions are reported voluntarily from a population of uncertain size, it is not always possible to reliably estimate their frequency.

•
Hemorrhage – Hemorrhage is the chief complication that may result from heparin therapy [see WARNINGS AND PRECAUTIONS 5-(5.2)]. Gastrointestinal or urinary tract bleeding during anticoagulant therapy may indicate the presence of an underlying occult lesion. Bleeding can occur at any site but certain specific hemorrhagic complications may be difficult to detect:

–
Adrenal hemorrhage, with resultant acute adrenal insufficiency, has occurred with heparin therapy, including fatal cases. Ovarian (corpus luteum) hemorrhage developed in a number of women of reproductive age receiving short- or long-term anticoagulant therapy.
–
Retroperitoneal hemorrhage.

•
Heparin-induced Thrombocytopenia (HIT) (With or Without Thrombosis) and Thrombocytopenia: [see WARNINGS AND PRECAUTIONS 5-(5.3 and 5.4)]
•
Hypersensitivity – Generalized hypersensitivity reactions have been reported with chills, fever, and urticaria as the most usual manifestations, and asthma, rhinitis, lacrimation, headache, nausea and vomiting, and anaphylactoid reactions, including shock, occurring more rarely. Itching and burning, especially on the plantar site of the feet, may occur [see WARNINGS AND PRECAUTIONS 5-(5.7)].
•
Elevations of serum aminotransferases – Significant elevations of aspartate aminotransferase (AST) and alanine aminotransferase (ALT) levels have occurred in patients who have received heparin.
•
Others – Osteoporosis following long-term administration of high-doses of heparin, cutaneous necrosis after systemic administration, suppression of aldosterone synthesis, delayed transient alopecia, priapism, and rebound hyperlipemia on discontinuation of heparin sodium have also been reported.

7 DRUG INTERACTIONS

7.1 Oral Anticoagulants

Heparin sodium may prolong the one-stage prothrombin time. Therefore, when heparin sodium is given with dicumarol or warfarin sodium, a period of at least 5 hours after the last intravenous dose or 24 hours after the last subcutaneous dose should elapse before blood is drawn if a valid prothrombin time is to be obtained.

7.2 Platelet Inhibitors

Drugs such as acetylsalicylic acid, dextran, phenylbutazone, ibuprofen, indomethacin, dipyridamole, hydroxychloroquine and others that interfere with platelet-aggregation reactions (the main hemostatic defense of heparinized patients) may induce bleeding and should be used with caution in patients receiving heparin sodium.

7.3 Other Interactions

Digitalis, tetracyclines, nicotine, or antihistamines, or intravenous (IV) nitroglycerin may partially counteract the anticoagulant action of heparin sodium.

7.4 Drug/Laboratory Test Interactions

Prothrombin time – Heparin sodium may prolong the one-stage prothrombin time. Therefore, when heparin sodium is given with warfarin, allow a period of at least 5 hours after the last intravenous dose or 24 hours after the last subcutaneous dose of heparin to elapse before blood is drawn to obtain a valid prothrombin time.

8 USE IN SPECIFIC POPULATIONS

8.1 Pregnancy

Risk Summary

In published reports, heparin exposure during pregnancy did not show evidence of an increased risk of adverse maternal or fetal outcomes in humans. No teratogenicity was observed in animal reproduction studies with administration of heparin sodium to pregnant rats and rabbits during organogenesis at doses up to 10,000 units/kg/day, approximately 10 times the maximum recommended human dose (MRHD) of 40,000 units/24 hours infusion [see Data]. In pregnant animals, doses up to10 times higher than the maximum human daily dose based on body weight resulted in increased resorptions. Consider the benefits and risks of HEPARIN SODIUM IN 0.45% SODIUM CHLORIDE INJECTION to a pregnant woman and possible risks to the fetus when prescribing HEPARIN SODIUM IN 0.45% SODIUM CHLORIDE INJECTION.

In the U.S. general population, the estimated background risk of major birth defects and miscarriage in clinically recognized pregnancies is 2-4% and 15-20%, respectively.

Data

Human Data

The maternal and fetal outcomes associated with uses of heparin via various dosing methods and administration routes during pregnancy have been investigated in numerous studies. These studies generally reported normal deliveries with no maternal or fetal bleeding and no other complications.

Animal Data

In a published study conducted in rats and rabbits, pregnant animals received heparin intravenously during organogenesis at a dose of 10,000 units/kg/day, approximately 10 times the maximum human daily dose based on body weight. The number of early resorptions increased in both species. There was no evidence of teratogenic effects.

8.2 Lactation

Risk Summary

There is no information regarding the presence of HEPARIN SODIUM IN 0.45% SODIUM CHLORIDE INJECTION in human milk, the effects on the breastfed infant, or the effects on milk production. Due to its large molecular weight, heparin is not likely to be excreted in human milk, and any heparin in milk would not be orally absorbed by a nursing infant. The developmental and health benefits of breastfeeding should be considered along with the mother's clinical need for HEPARIN SODIUM IN 0.45% SODIUM CHLORIDE INJECTION and any potential adverse effects on the breastfed infant from HEPARIN SODIUM IN 0.45% SODIUM CHLORIDE INJECTION or from the underlying maternal condition [see USE IN SPECIFIC POPULATIONS 8-(8.4)].

8.4 Pediatric Use

There are no adequate and well controlled studies on heparin use in pediatric patients. Pediatric dosing recommendations are based on clinical experience [see DOSAGE AND ADMINISTRATION 2-(2.4)].

8.5 Geriatric Use

There are limited adequate and well-controlled studies in patients 65 years and older. However, a higher incidence of bleeding has been reported in patients over 60 years of age, especially women [see WARNINGS AND PRECAUTIONS 5-(5.2)]. Lower doses of heparin may be indicated in these patients [see CLINICAL PHARMACOLOGY 12-(12.3)].

10 OVERDOSAGE

Bleeding is the chief sign of heparin overdosage.

Neutralization of heparin effect.

When clinical circumstances (bleeding) require reversal of heparinization, protamine sulfate (1% solution) by slow infusion will neutralize heparin sodium. No more than 50 mg should be administered, very slowly in any 10 minute period. Each mg of protamine sulfate neutralizes approximately 100 USP Heparin Units. The amount of protamine required decreases over time as heparin is metabolized. Although the metabolism of heparin is complex, it may, for the purpose of choosing a protamine dose, be assumed to have a half-life of about ½ hour after intravenous injection.

Because fatal reactions often resembling anaphylaxis have been reported, the drug should be given only when resuscitation techniques and treatment of anaphylactoid shock are readily available.

For additional information, consult the prescribing information for Protamine Sulfate Injection, USP.

11 DESCRIPTION

Heparin is a heterogeneous group of straight-chain anionic mucopolysaccharides, called glycosaminoglycans possessing anticoagulant properties. It is composed of polymers of alternating derivations of α-D-glucosamido (N-Sulfated O-Sulfated or N-acetylated) and O-sulfated uronic acid (α-L-iduronic acid or β-D-glucoronic acid).

Structure of Heparin Sodium (representative subunits):

HEPARIN SODIUM IN 0.45% SODIUM CHLORIDE INJECTION is a sterile preparation of heparin sodium (derived from porcine intestinal mucosa) for intravenous administration. It contains no bacteriostatic or antimicrobial agent or added buffer. The solution may contain sodium hydroxide and/or hydrochloric acid for pH adjustment. The pH range is 6.1 (5.0 – 7.5) and the osmolarity mOsmol/L (calc.) is 155. The potency is determined by a biological assay using a USP reference standard based on units of heparin activity per milligram.

Each mL of the 50 USP units per mL preparations contains: 50 USP units of heparin sodium, 4.5 mg sodium chloride and 0.1 mg edetate disodium, anhydrous added as a stabilizer.

Each mL of the 100 USP units per mL preparations contains: 100 USP units of heparin sodium, 4.5 mg sodium chloride and 0.1 mg edetate disodium, anhydrous added as a stabilizer

12 CLINICAL PHARMACOLOGY

12.1 Mechanism of Action

Heparin inhibits reactions that lead to the clotting of blood and the formation of fibrin clots both in vitro and in vivo. Heparin acts at multiple sites in the normal coagulation system. Small amounts of heparin in combination with antithrombin III (heparin cofactor) can inhibit thrombosis by inactivating activated Factor X and inhibiting the conversion of prothrombin to thrombin. Once active thrombosis has developed, larger amounts of heparin can inhibit further coagulation by inactivating thrombin and preventing the conversion of fibrinogen to fibrin. Heparin also prevents the formation of a stable fibrin clot by inhibiting the activation of the fibrin stabilizing factor. Heparin does not have fibrinolytic activity; therefore, it will not lyse existing clots.

12.2 Pharmacodynamics

Bleeding time is usually unaffected by heparin. Clotting time is prolonged by full therapeutic doses of heparin; in most cases it is not measurably affected by low doses of heparin.

12.3 Pharmacokinetics

Peak plasma levels of heparin are achieved 2 to 4 hours following subcutaneous administration, although there are considerable individual variations. Loglinear plots of heparin plasma concentrations with time for a wide range of dose levels are linear which suggests the absence of zero order processes. Liver and the reticuloendothelial system are the sites of biotransformation. The biphasic elimination curve, a rapidly declining alpha phase (t½ = 10 minutes) and after the age of 40 a slower beta phase, indicates uptake in organs. The absence of a relationship between anticoagulant half-life and concentration half-life may reflect factors such as protein binding of heparin.

Patients over 60 years of age, following similar doses of heparin, may have higher plasma levels of heparin and longer activated partial thromboplastin times (APTTs) compared with patients under 60 years of age [see USE IN SPECIFIC POPULATIONS 8-(8.5)].

13 NONCLINICAL TOXICOLOGY

13.1 Carcinogenesis, Mutagenesis, Impairment of Fertility

Long term studies in animals to evaluate the carcinogenic potential, reproduction studies in animals to determine effects on fertility of males and females, and studies to determine mutagenic potential have not been conducted.

16 HOW SUPPLIED/STORAGE AND HANDLING

HEPARIN SODIUM IN 0.45% SODIUM CHLORIDE is supplied in the following dosage forms.
NDC 51662-1411-1
HEPARIN SODIUM IN 0.45% SODIUM CHLORIDE INJECTION (100 USP UNITS/mL) 250 mL

HF Acquisition Co LLC, DBA HealthFirst
Mukilteo, WA 98275

Also supplied in the following manufacture supplied dosage forms

Intravenous solutions with heparin sodium are supplied in single-dose flexible plastic containers in varied sizes and concentrations as shown in the accompanying Table.

Store at 20 to 25°C (68 to 77°F). [See USP Controlled Room Temperature.] Protect from freezing.

HEPARIN SODIUM IN 0.45% SODIUM CHLORIDE is supplied in the following dosage forms.
NDC 51662-1411-2
HEPARIN SODIUM IN 0.45% SODIUM CHLORIDE INJECTION (100 USP UNITS/mL) 250 mL

HF Acquisition Co LLC, DBA HealthFirst
Mukilteo, WA 98275

Also supplied in the following manufacture supplied dosage forms

Intravenous solutions with heparin sodium are supplied in single-dose flexible plastic containers in varied sizes and concentrations.

Store at 20 to 25°C (68 to 77°F). [See USP Controlled Room Temperature.] Protect from freezing.

HEPARIN SODIUM IN 0.45% SODIUM CHLORIDE is supplied in the following dosage forms.
NDC 51662-1411-3
HEPARIN SODIUM IN 0.45% SODIUM CHLORIDE INJECTION (100 USP UNITS/mL) 250 mL

HF Acquisition Co LLC, DBA HealthFirst
Mukilteo, WA 98275

Also supplied in the following manufacture supplied dosage forms

Intravenous solutions with heparin sodium are supplied in single-dose flexible plastic containers in varied sizes and concentrations.

Store at 20 to 25°C (68 to 77°F). [See USP Controlled Room Temperature.] Protect from freezing.

17 PATIENT COUNSELING INFORMATION

Hemorrhage

Inform patients that it may take them longer than usual to stop bleeding, that they may bruise and/or bleed more easily when they are treated with heparin, and that they should report any unusual bleeding or bruising to their physician. Hemorrhage can occur at virtually any site in patients receiving heparin. Fatal hemorrhages have occurred [see WARNINGS AND PRECAUTIONS 5-(5.2)].

Prior to Surgery

Advise patients to inform physicians and dentists that they are receiving heparin before any surgery is scheduled [see WARNINGS AND PRECAUTIONS 5-(5.2)].

Heparin-Induced Thrombocytopenia

Inform patients of the risk of heparin-induced thrombocytopenia (HIT). HIT may progress to the development of venous and arterial thromboses, a condition known as heparin-induced thrombocytopenia and thrombosis. HIT (With or Without Thrombosis) can occur up to several weeks after the discontinuation of heparin therapy [see WARNINGS AND PRECAUTIONS 5-(5.3 and 5.4)].

Hypersensitivity

Inform patients that generalized hypersensitivity reactions have been reported. Necrosis of the skin has been reported at the site of subcutaneous injection of heparin [see WARNINGS AND PRECAUTIONS 5-(5.7), ADVERSE REACTIONS (6)].

Other Medications

Because of the risk of hemorrhage, advise patients to inform their physicians and dentists of all medications they are taking, including non-prescription medications, and before starting any new medication [see DRUG INTERACTIONS 7-(7.2)].
EN-4244

Hospira, Inc., Lake Forest, IL 60045 USA

PRINCIPAL DISPLAY PANEL, POUCH LABEL

51662-1411-2 Pouch Label

PRINCIPAL DISPLAY PANEL, CASE LABEL

51662-1411-3 CASE LABEL